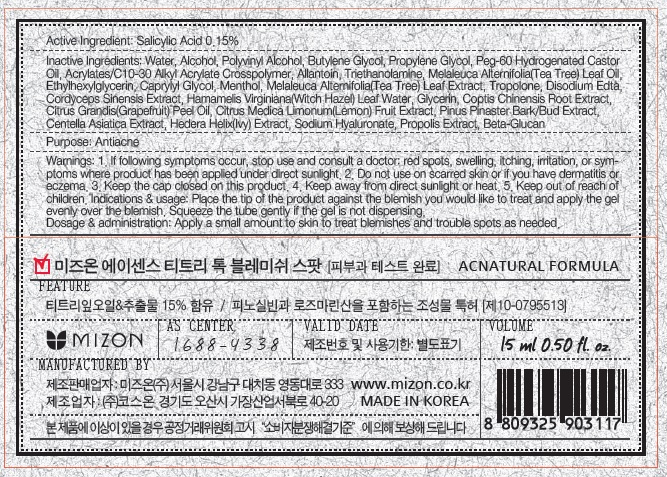 DRUG LABEL: ACENCE TEA TREE TOCK BLEMISH SPOT
NDC: 57718-090 | Form: SOLUTION
Manufacturer: MIZON CO., LTD.
Category: otc | Type: HUMAN OTC DRUG LABEL
Date: 20160122

ACTIVE INGREDIENTS: Salicylic Acid 22.5 mg/15 mL
INACTIVE INGREDIENTS: Water; Alcohol

ACTIVE INGREDIENT

Active Ingredient: Salicylic Acid 0.15%

INACTIVE INGREDIENT

Inactive Ingredients: Water, Alcohol, Polyvinyl Alcohol, Butylene Glycol, Propylene Glycol, Peg-60 Hydrogenated Castor Oil, Acrylates/C10-30 Alkyl Acrylate Crosspolymer, Allantoin, Triethanolamine, Melaleuca Alternifolia(Tea Tree) Leaf Oil, Ethylhexylglycerin, Caprylyl Glycol, Menthol, Melaleuca Alternifolia(Tea Tree) Leaf Extract, Tropolone, Disodium Edta, Cordyceps Sinensis Extract, Hamamelis Virginiana(Witch Hazel) Leaf Water, Glycerin, Coptis Chinensis Root Extract, Citrus Grandis(Grapefruit) Peel Oil, Citrus Medica Limonum(Lemon) Fruit Extract, Pinus Pinaster Bark/Bud Extract, Centella Asiatica Extract, Hedera Helix(Ivy) Extract, Sodium Hyaluronate, Propolis Extract, Beta-Glucan

PURPOSE

Purpose: Antiacne

WARNINGS

Warnings: 1. If following symptoms occur, stop use and consult a doctor: red spots, swelling, itching, irritation, or symptoms where product has been applied under direct sunlight. 2. Do not use on scarred skin or if you have dermatitis or eczema. 3. Keep the cap closed on this product. 4. Keep away from direct sunlight or heat. 5. Keep out of reach of children.

KEEP OUT OF REACH OF CHILDREN

Indications & usage

Indications & usage: Place the tip of the product against the blemish you would like to treat and apply the gel evenly over the blemish. Squeeze the tube gently if the gel is not dispensing.

DOSAGE & ADMINISTRATION

Dosage & administration: Apply a small amount to skin to treat blemishes and trouble spots as needed.